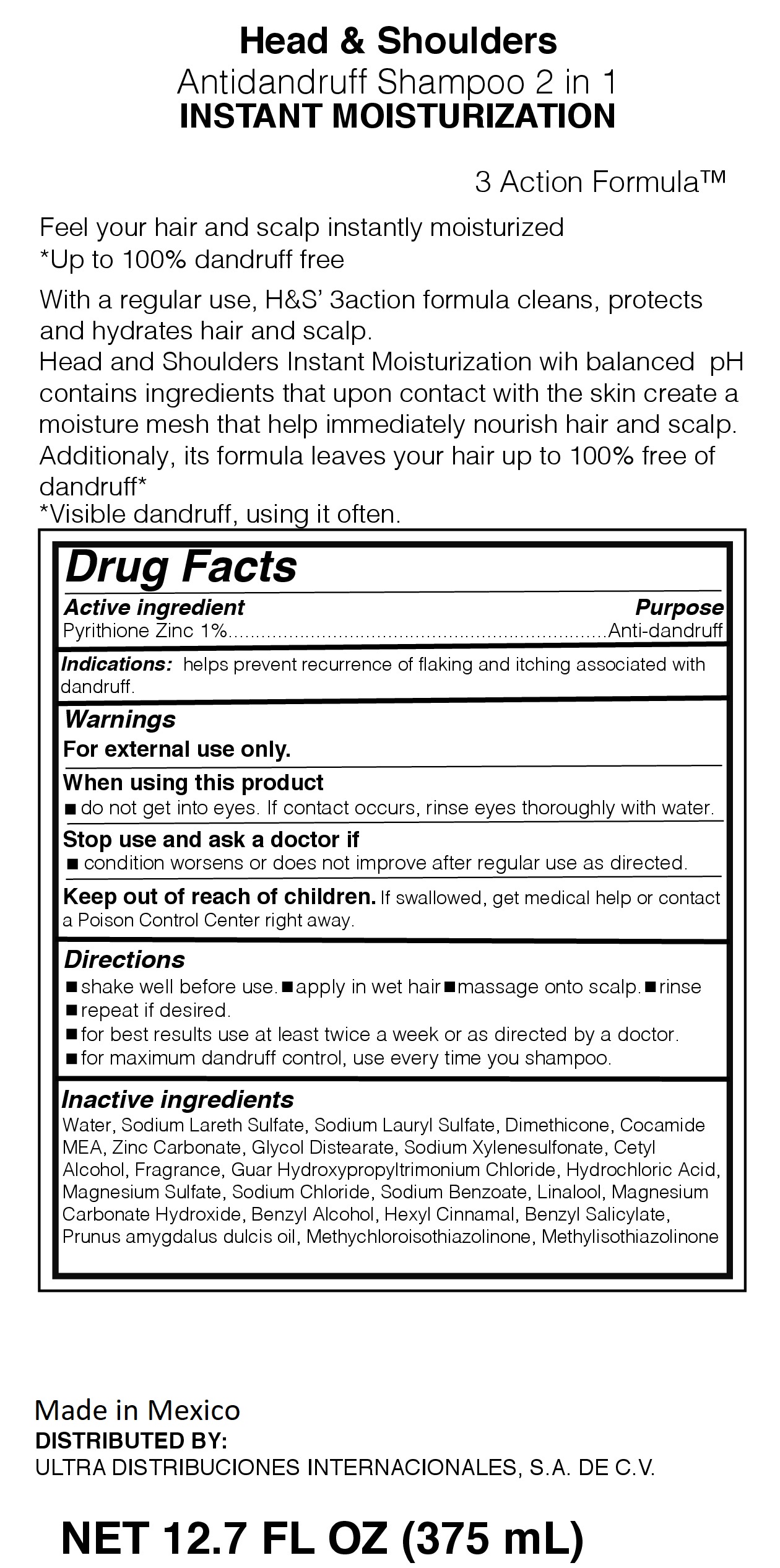 DRUG LABEL: HEAD AND SHOULDERS 2 IN 1 INSTANT MOISTURIZATION
NDC: 72389-105 | Form: LOTION/SHAMPOO
Manufacturer: ULTRA DISTRIBUCIONES INTERNACIONALES, S.A. DE C.V.
Category: otc | Type: HUMAN OTC DRUG LABEL
Date: 20220114

ACTIVE INGREDIENTS: PYRITHIONE ZINC 1 g/100 mL
INACTIVE INGREDIENTS: CETYL ALCOHOL; BENZYL SALICYLATE; WATER; SODIUM LAURYL SULFATE; SODIUM LAURETH SULFATE; GLYCOL DISTEARATE; MAGNESIUM CARBONATE HYDROXIDE; DIMETHICONE; .ALPHA.-HEXYLCINNAMALDEHYDE; SODIUM CHLORIDE; COCO MONOETHANOLAMIDE; METHYLISOTHIAZOLINONE; SODIUM BENZOATE; GUAR HYDROXYPROPYLTRIMONIUM CHLORIDE (1.7 SUBSTITUENTS PER SACCHARIDE); HYDROCHLORIC ACID; ZINC CARBONATE; METHYLCHLOROISOTHIAZOLINONE; SODIUM XYLENESULFONATE; MAGNESIUM SULFATE, UNSPECIFIED FORM; LINALOOL, (+)-; BENZYL ALCOHOL; ALMOND OIL

Head and Shoulders 2 in 1 INSTANT MOISTURIZATION

Purpose

Feel your hair and scalp instantly moisturized

*Up to 100% dandruff free

With Regular use, H&S' 3action formula cleans, protects and hydrates hair and scalp.

Head and Shoulders Instant Moisturization with balanced PH contains ingredients that upon contact with the skin create a moisture mesh that help immediately nourish hair and scalp.

Additionally, its formula leaves your hair up to 100% free of dandruff*

*Visible dandruff, using it often.

Active Ingredient

Active Ingredient................................................................................Purpose

Pyrithione Zinc 1%.....................................................................Anti-dandruff

Warnings

for external use only.

When using this product

-do not get into eyes. If contact occurs, rinse thoroughly with water

Stop use and ask doctor if

condition worsens or does not improve after regular use as directed

Keep our of reach of children

If swallowed, get medical help or contact a Poison Control Center right away

Directions

-shake well before use - apply in wet hair - massage into scalp - rinse

-repeat as desired

-for best results use at least twice a week or as directed by a doctor

-for maximum dandruff control, use every time you shampoo

Inactive Ingredients

Water, Sodium Laureth Sulfate, Sodium Lauryl Sulfate, Dimethicone, Cocamide MEA, Zinc Carbonate, Glycol Distearate, Sodium Xylenesulfonate, Cetyl Alcohol, Fragrance, Guar Hydroxypropyltrimonium Chloride, Hydrochloric Acid, Magnesium Sulfate, Sodium Chloride, Sodium Benzoate, Linalool, Magnesium Carbonate Hydroxide, Benzyl Alcohol, Hexyl Cinnamal, Benzyl Salicylate, Prunus amygdalus dulcis oil, Methylchloroisothiazolinone, Methylisothiaolinone

Distributed by:

ULTRA DISTRIBUCIONES INTERNACIONALES, S.A. DE C.V.

Made in Mexico

Indications:

helps prevent recurrence of flaking and itching associated with dandruff

Principal Display Panel Antidandruff Shampoo 2 in 1 INSTANT MOISTURIZATION

INSTANT MOISTURIZATION